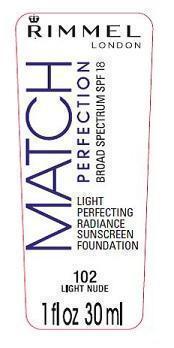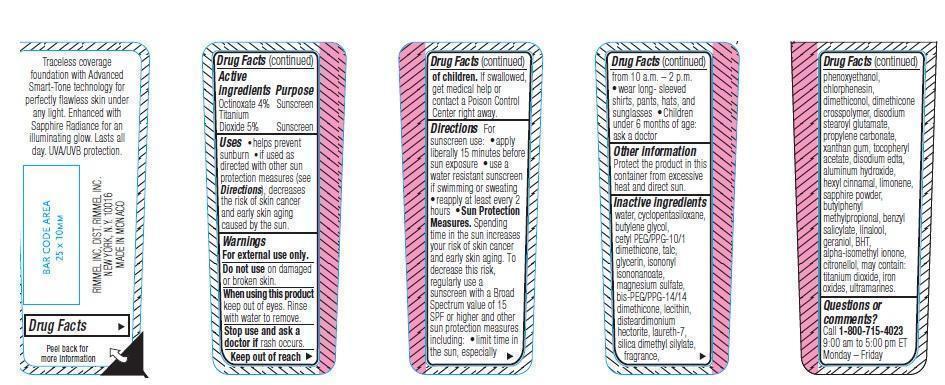 DRUG LABEL: Match Perfection SPF 18
NDC: 76485-1028 | Form: LIQUID
Manufacturer: Rimmel Inc.
Category: otc | Type: HUMAN OTC DRUG LABEL
Date: 20121018

ACTIVE INGREDIENTS: OCTINOXATE 1.2 mL/30 mL; TITANIUM DIOXIDE 1.5 mL/30 mL
INACTIVE INGREDIENTS: Water; CYCLOMETHICONE 5; BUTYLENE GLYCOL; CETYL PEG/PPG-10/1 DIMETHICONE (HLB 1.5); TALC; GLYCERIN; ISONONYL ISONONANOATE; MAGNESIUM SULFATE; LAURETH-7; SILICA DIMETHYL SILYLATE; PHENOXYETHANOL; CHLORPHENESIN; DISODIUM STEAROYL GLUTAMATE; PROPYLENE CARBONATE; XANTHAN GUM; .ALPHA.-TOCOPHEROL ACETATE; EDETATE DISODIUM; ALUMINUM HYDROXIDE; .ALPHA.-HEXYLCINNAMALDEHYDE; BUTYLPHENYL METHYLPROPIONAL; BENZYL SALICYLATE; LINALOOL, (+/-)-; GERANIOL; BUTYLATED HYDROXYTOLUENE; ISOMETHYL-.ALPHA.-IONONE; .BETA.-CITRONELLOL, (R)-; TITANIUM DIOXIDE; FERRIC OXIDE RED

Drug Facts

ACTIVE INGREDIENT

Octinoxate 4%

Titanium Dioxide 4%

PURPOSE

Sunscreen

Keep out of reach of children. If swallowed, get medical help or contact a Poison Control Center right away.

INDICATIONS AND USAGE

Helps prevent sunburn. If used as directed with other sun protection measures (see Directions), decreases the risk of skin cancer and early skin aging caused by the sun.

WARNINGS

For external use only.

Do not use on damaged or broken skin.

When using this product keep out of eyes. Rinse with water to remove.

Stop use and ask a doctor if rash occurs.

DOSAGE AND ADMINISTRATION

Directions. For sunscreen use: apply liberally 15 minutes before sun exposure. Use a water resistant sunscreen if swimming or sweating. Reapply at least every 2 hours.

Sun Protection Measures. Spending time in the sun increases your risk of skin cancer and early skin aging. To decrease this risk, regularly use a sunscreen with a Broad Spectrum value of 15 SPF or higher and other sun protection measures including:

- limit time in the sun, especially from 10 a.m.-2 p.m.
- wear long-sleeved shirts, pants, hats and sunglasses
- children under 6 months of age: ask a doctor

OTHER SAFETY INFORMATION

Protect the product in this container from excessive heat and direct sun.

INACTIVE INGREDIENT

water, cyclopentasiloxane, butylene glycol, cetyl PEG/PPG-10/1 dimethicone, talc, glycerin, isononyl isononanoate, magnesium sulfate, bis-PEG/PPG-14/14 dimethicone, lecithin, disteardimonium hectorite, laureth-7, silica dimethyl silylate, fragrance, phenoxyethanol, chlorphenesin, dimethiconol, dimethicone crosspolymer, disodium stearoyl glutamate, propylene carbonate, xanthan gum, tocopheryl acetate, disodium edta, aluminum hydroxide, hexyl cinnamal, limonene, sapphare powder, butylphenyl methylpropional, benzyl salicylate, linalool, geraniol, BHT, alpha-isomethyl ionone, citronellol, may contain: titanium dioxide, iron oxides, ultramarines.